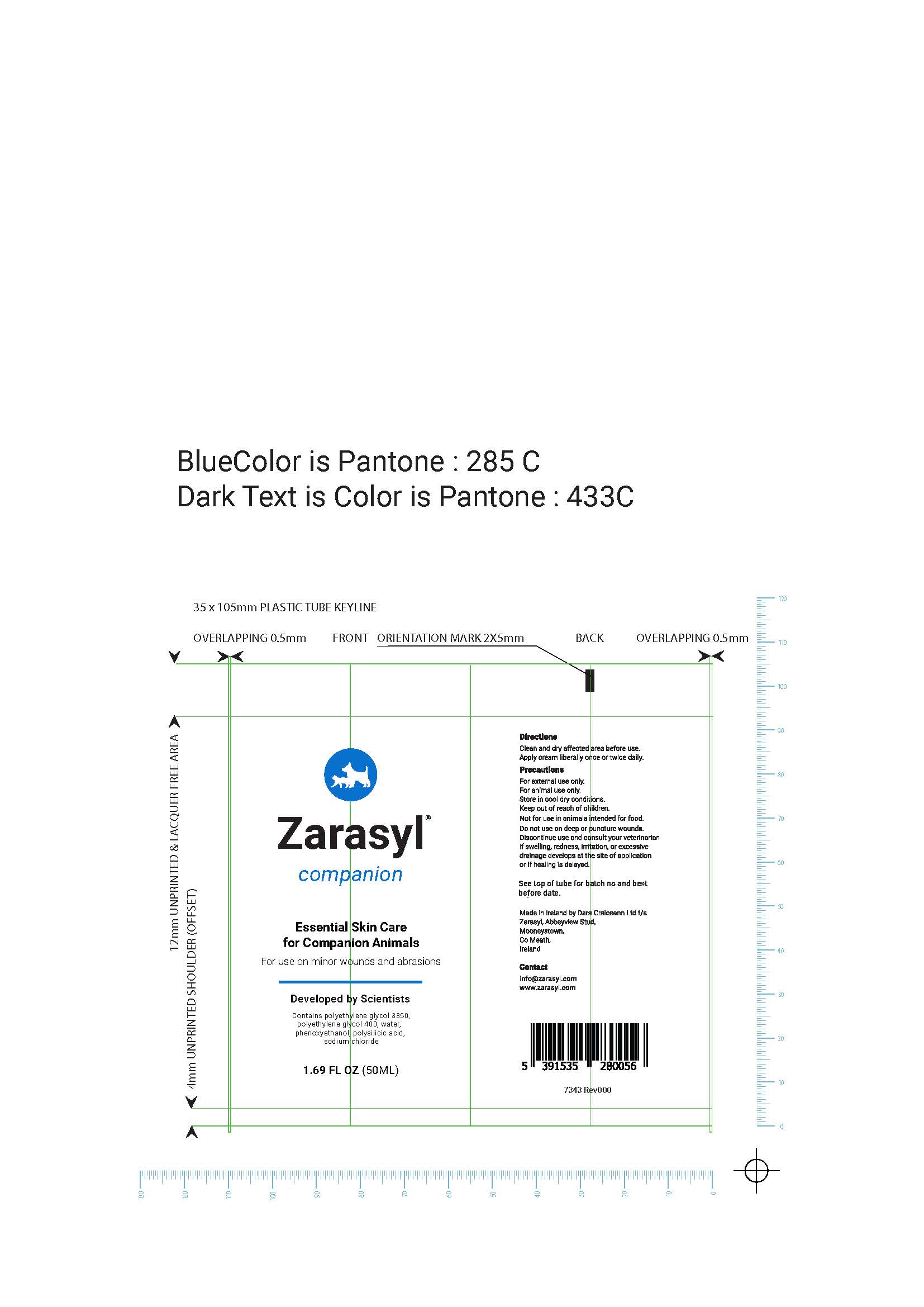 DRUG LABEL: Zarasyl Companion
NDC: 86107-002 | Form: CREAM
Manufacturer: Dara Craiceann Limited
Category: animal | Type: OTC ANIMAL DRUG LABEL
Date: 20220727

ACTIVE INGREDIENTS: HYDRATED SILICA 0.074 g/50 mL
INACTIVE INGREDIENTS: Water; POLYETHYLENE GLYCOL 3350; POLYETHYLENE GLYCOL 400; SODIUM CHLORIDE; PHENOXYETHANOL

PRECAUTIONS

For external use only.
For animal use only.

Store in cool dry conditions.

Keep out of reach of children.

Not for use in animals intended for food.
Do not use on deep or puncture wounds

Discontinue use and consult your veterinarian if swelling, redness, irritation or excessive drainage develops at the site of application or if healing is delayed

INSTRUCTIONS FOR USE

Clean and dry affected area before use. Apply cream liberally once or twice daily.